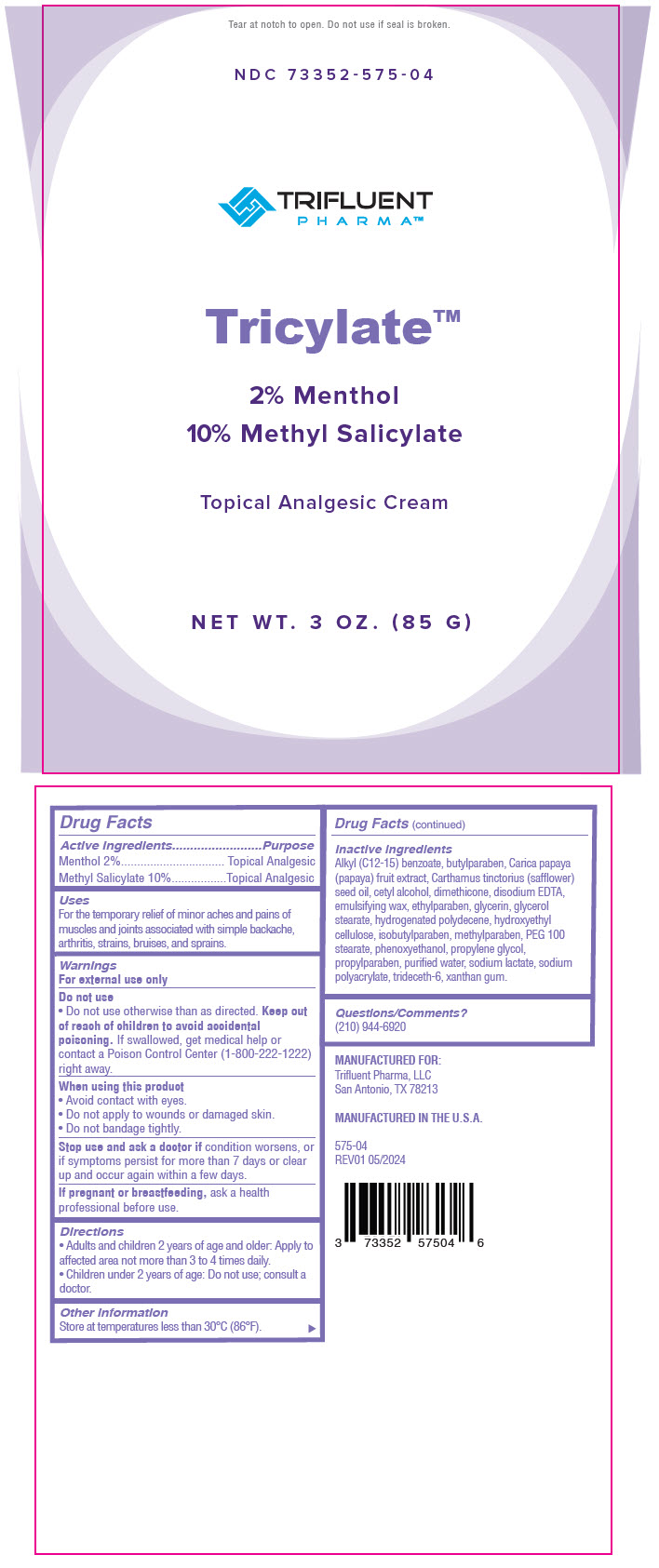 DRUG LABEL: Tricylate
NDC: 73352-575 | Form: CREAM
Manufacturer: Trifluent Pharma LLC
Category: otc | Type: HUMAN OTC DRUG LABEL
Date: 20251013

ACTIVE INGREDIENTS: MENTHOL, UNSPECIFIED FORM 20 mg/1 g; METHYL SALICYLATE 100 mg/1 g
INACTIVE INGREDIENTS: ALKYL (C12-15) BENZOATE; BUTYLPARABEN; PAPAYA; SAFFLOWER OIL; CETYL ALCOHOL; DIMETHICONE, UNSPECIFIED; EDETATE DISODIUM; ETHYLPARABEN; GLYCERIN; GLYCERYL MONOSTEARATE; PEG-100 MONOSTEARATE; HYDROGENATED POLYDECENE TYPE I; HYDROXYETHYL CELLULOSE, UNSPECIFIED; ISOBUTYLPARABEN; METHYLPARABEN; PHENOXYETHANOL; PROPYLENE GLYCOL; PROPYLPARABEN; WATER; SODIUM LACTATE; SODIUM POLYACRYLATE (2500000 MW); TRIDECETH-6; XANTHAN GUM

TRICYLATE™

Drug Facts

ACTIVE INGREDIENT

Active ingredients | Purpose
Menthol 2% | Topical Analgesic
Methyl Salicylate 10% | Topical Analgesic

Uses

For the temporary relief of minor aches and pains of muscles and joints associated with simple backache, arthritis, strains, bruises, and sprains.

Warnings

For external use only

- Do not use otherwise than as directed.

Keep out of reach of children to avoid accidental poisoning. If swallowed, get medical help or contact a Poison Control Center (1-800-222-1222) right away.

When using this product

- Avoid contact with eyes.
- Do not apply to wounds or damaged skin.
- Do not bandage tightly.

Stop use and ask a doctor if condition worsens, or if symptoms persist for more than 7 days or clear up and occur again within a few days.

PREGNANCY OR BREAST FEEDING

If pregnant or breastfeeding, ask a health professional before use.

Directions

- Adults and children 2 years of age and older: Apply to affected area not more than 3 to 4 times daily.
- Children under 2 years of age: Do not use; consult a doctor.

Other information

Store at temperatures less than 30°C (86°F).

Inactive ingredients

Alkyl (C12-15) benzoate, butylparaben, Carica papaya (papaya) fruit extract, Carthamus tinctorius (safflower) seed oil, cetyl alcohol, dimethicone, disodium EDTA, emulsifying wax, ethylparaben, glycerin, glycerol stearate, hydrogenated polydecene, hydroxyethyl cellulose, isobutylparaben, methylparaben, PEG 100 stearate, phenoxyethanol, propylene glycol, propylparaben, purified water, sodium lactate, sodium polyacrylate, trideceth-6, xanthan gum.

Questions/Comments?

(210) 944-6920

PRINCIPAL DISPLAY PANEL - 85 G Pouch Tube Label

Tear at notch to open. Do not use if seal is broken.

NDC 73352-575-04

TRIFLUENT
PHARMA™

Tricylate™

2% Menthol
10% Methyl Salicylate

Topical Analgesic Cream

NET WT. 3 OZ. (85 G)